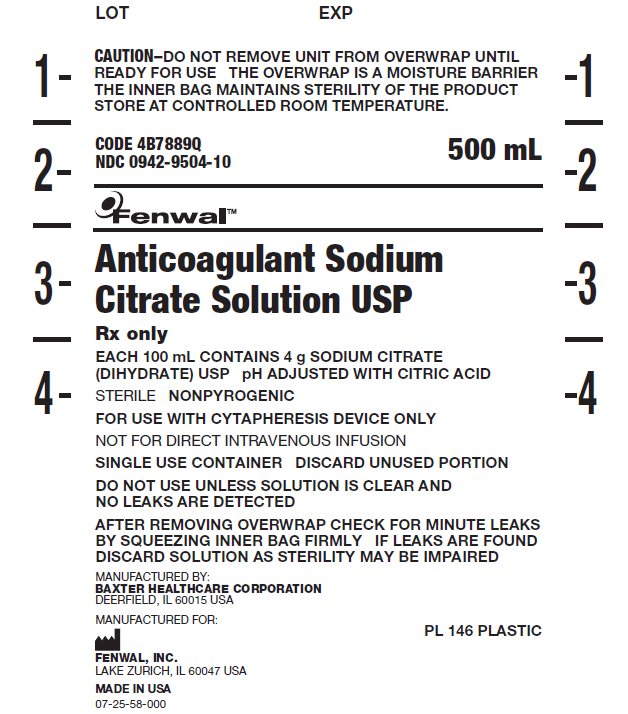 DRUG LABEL: Sodium Citrate Blood-Pack Units, (PL 146 Plastic)
NDC: 0942-9504 | Form: SOLUTION
Manufacturer: Fenwal, Inc.
Category: prescription | Type: HUMAN PRESCRIPTION DRUG LABEL
Date: 20220211

ACTIVE INGREDIENTS: TRISODIUM CITRATE DIHYDRATE 4 g/100 mL
INACTIVE INGREDIENTS: WATER; CITRIC ACID MONOHYDRATE

Anticoagulant Sodium Citrate Solution USP

Anticoagulant Sodium Citrate Solution USP

A standalone direction insert does not exist for this product.

PACKAGE/LABEL DISPLAY PANEL

CAUTION–DO NOT REMOVE UNIT FROM OVERWRAP UNTIL READY FOR USE
THE OVERWRAP IS A MOISTURE BARRIER
THE INNER BAG MAINTAINS STERILITY OF THE PRODUCT
STORE AT CONTROLLED ROOM TEMPERATURE.

CODE 4B7889Q

NDC 0942-9504-10

500 mL

Fenwal™

Anticoagulant Sodium Citrate Solution USP

Rx only

EACH 100 mL CONTAINS 4 g SODIUM CITRATE (DIHYDRATE) USP
pH ADJUSTED WITH CITRIC ACID

STERILE
NONPYROGENIC

FOR USE WITH CYTAPHERESIS DEVICE ONLY

NOT FOR DIRECT INTRAVENOUS INFUSION

SINGLE USE CONTAINER
DISCARD UNUSED PORTION

DO NOT USE UNLESS SOLUTION IS CLEAR AND NO LEAKS ARE DETECTED

AFTER REMOVING OVERWRAP CHECK FOR MINUTE LEAKS BY SQUEEZING INNER BAG FIRMLY
IF LEAKS ARE FOUND DISCARD SOLUTION AS STERILITY MAY BE IMPAIRED

MANUFACTURED BY:
BAXTER HEALTHCARE CORPORATION
DEERFIELD, IL 60015 USA

MANUFACTURED FOR:

FENWAL, INC.
LAKE ZURICH, IL 60047 USA

MADE IN USA
07-25-58-000

PL 146 PLASTIC